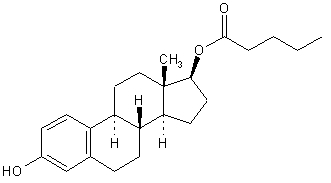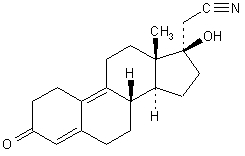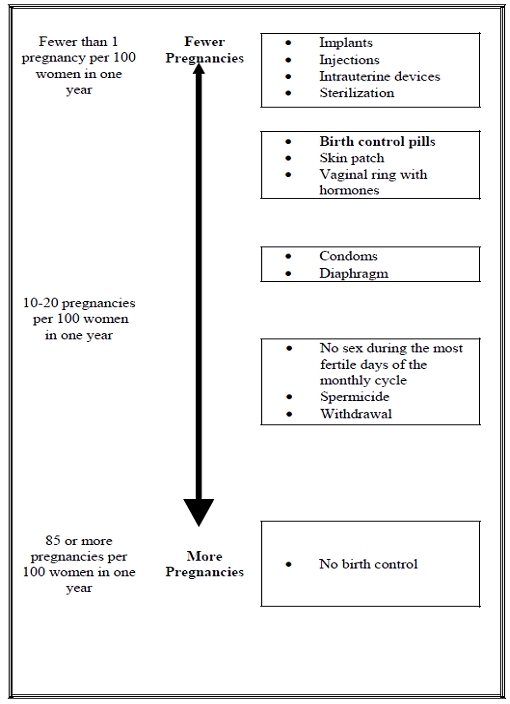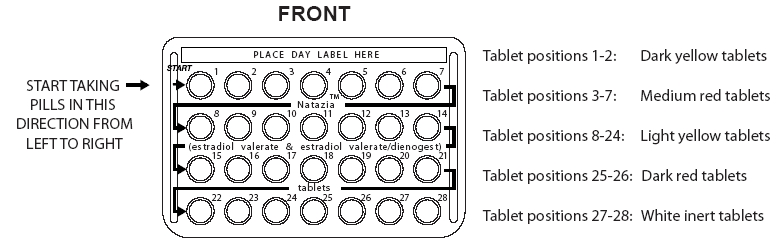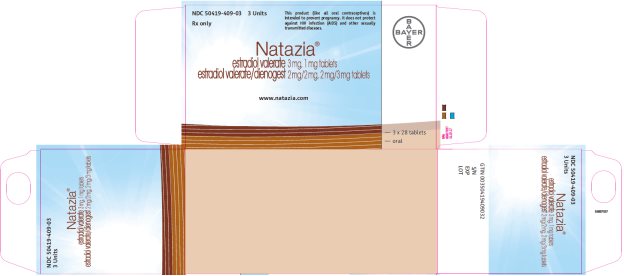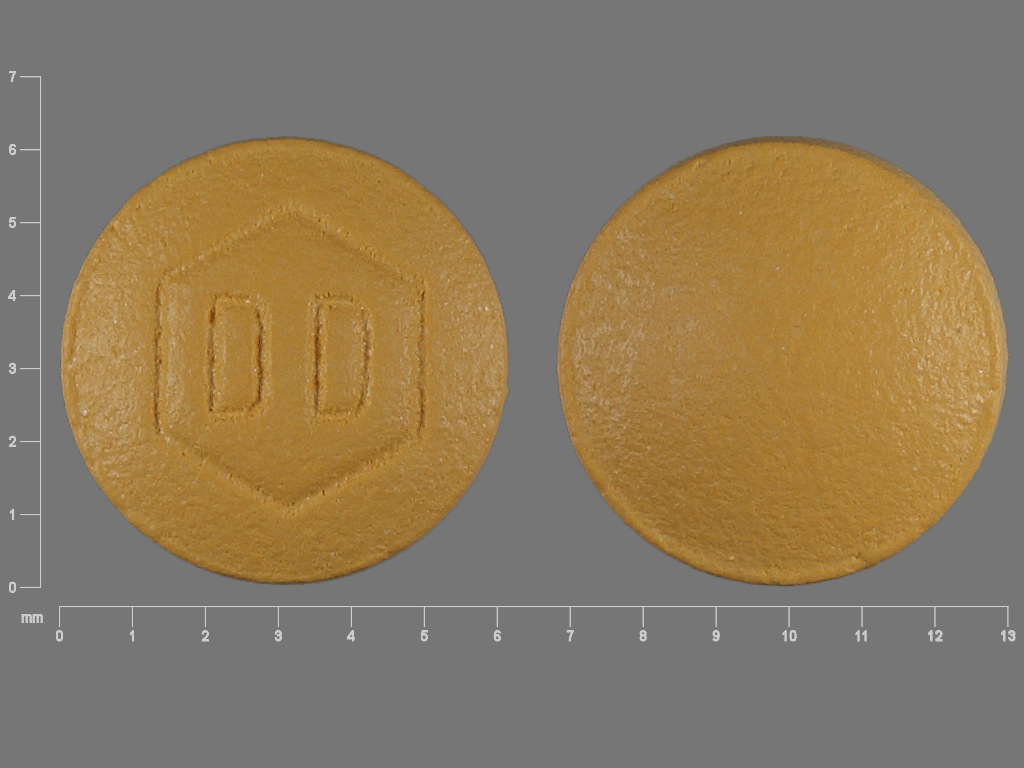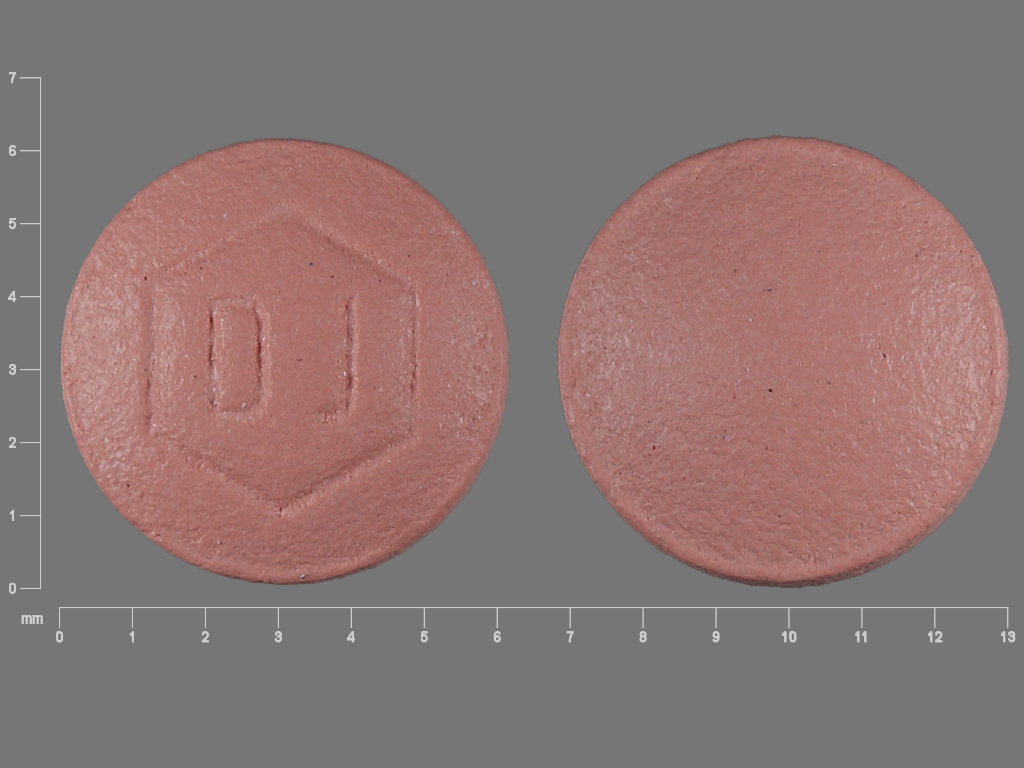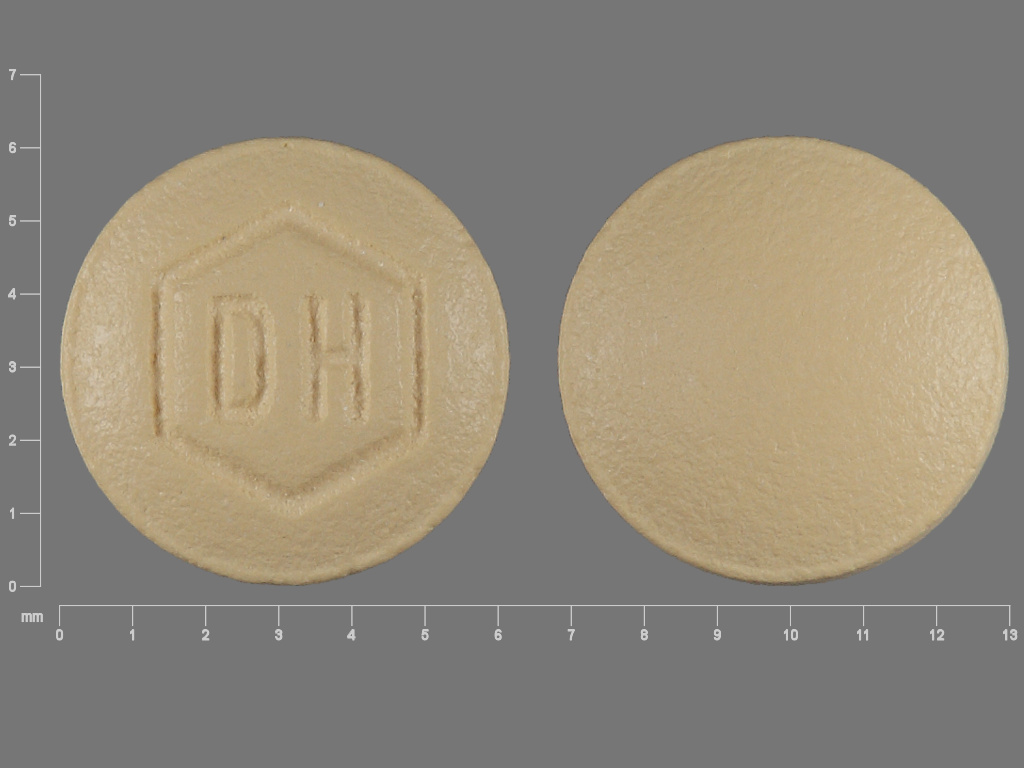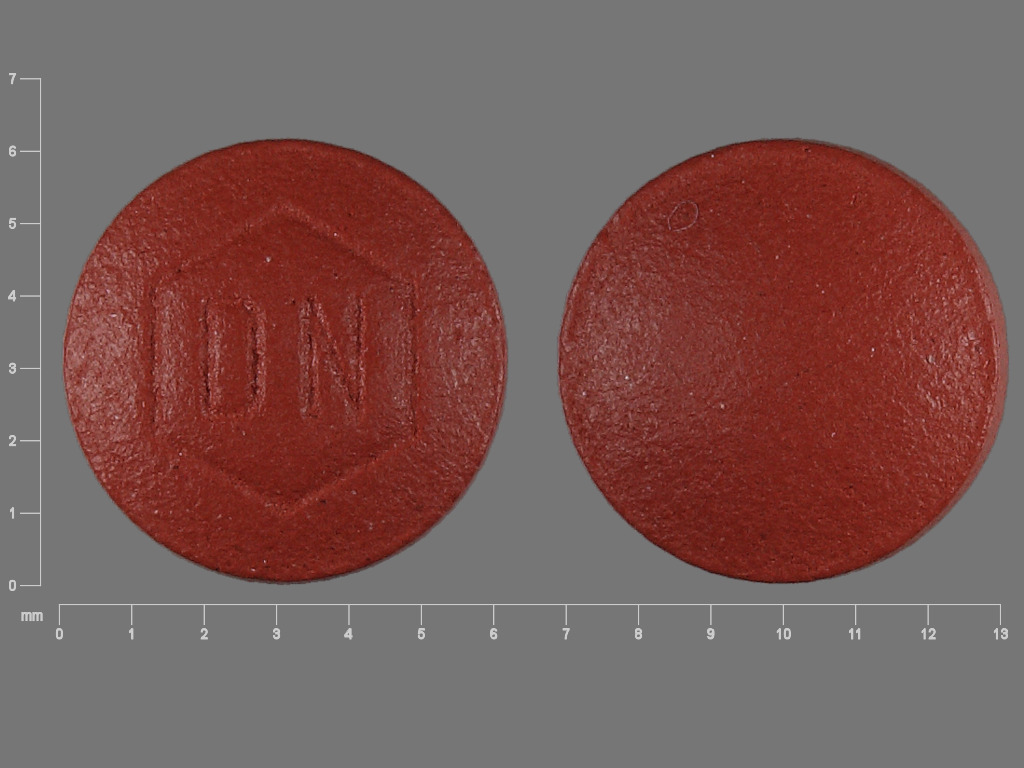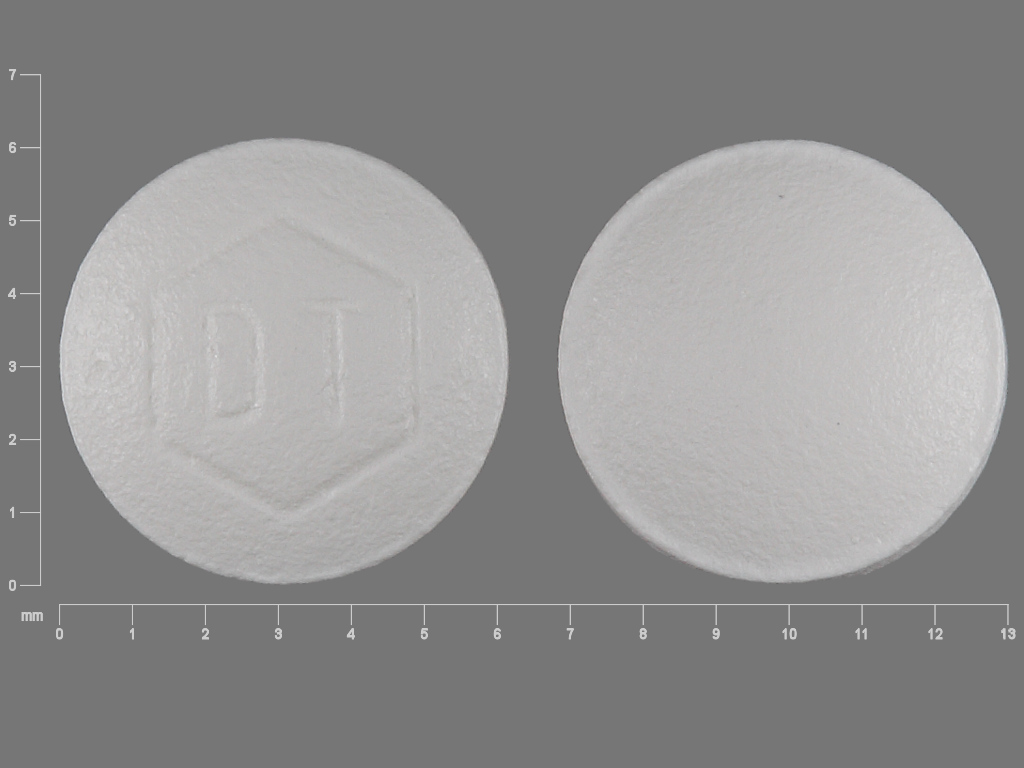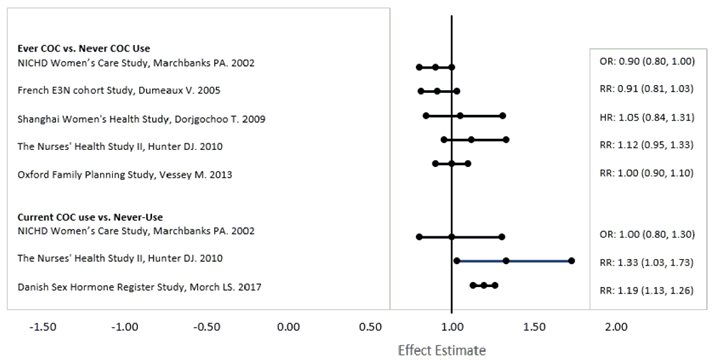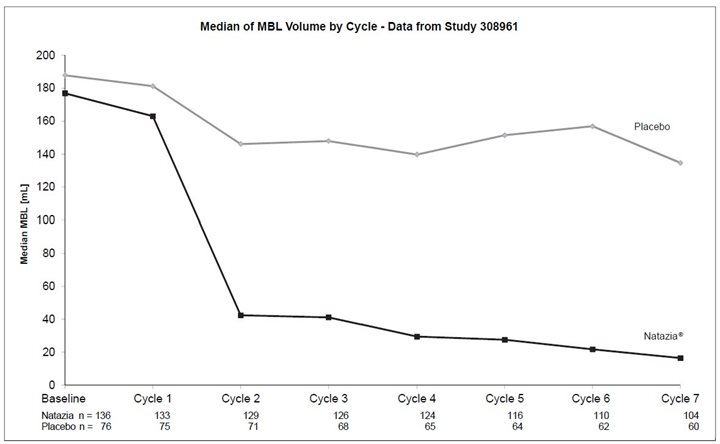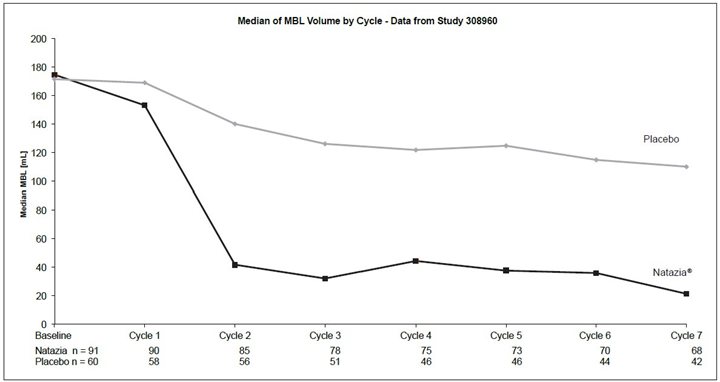 DRUG LABEL: Natazia
NDC: 50419-409 | Form: KIT | Route: ORAL
Manufacturer: Bayer HealthCare Pharmaceuticals Inc.
Category: prescription | Type: HUMAN PRESCRIPTION DRUG LABEL
Date: 20240626

ACTIVE INGREDIENTS: ESTRADIOL VALERATE 3 mg/1 1; ESTRADIOL VALERATE 2 mg/1 1; DIENOGEST 2 mg/1 1; ESTRADIOL VALERATE 2 mg/1 1; DIENOGEST 3 mg/1 1; ESTRADIOL VALERATE 1 mg/1 1
INACTIVE INGREDIENTS: FERRIC OXIDE YELLOW; LACTOSE MONOHYDRATE; POLYETHYLENE GLYCOL 6000; MAGNESIUM STEARATE; STARCH, CORN; POVIDONE K25; TALC; TITANIUM DIOXIDE; HYPROMELLOSE, UNSPECIFIED; FERRIC OXIDE RED; HYPROMELLOSE, UNSPECIFIED; LACTOSE MONOHYDRATE; POLYETHYLENE GLYCOL 6000; MAGNESIUM STEARATE; STARCH, CORN; POVIDONE K25; TALC; TITANIUM DIOXIDE; FERRIC OXIDE YELLOW; HYPROMELLOSE, UNSPECIFIED; LACTOSE MONOHYDRATE; POLYETHYLENE GLYCOL 6000; MAGNESIUM STEARATE; STARCH, CORN; POVIDONE K25; TALC; TITANIUM DIOXIDE; HYPROMELLOSE, UNSPECIFIED; LACTOSE MONOHYDRATE; POLYETHYLENE GLYCOL 6000; MAGNESIUM STEARATE; STARCH, CORN; TALC; TITANIUM DIOXIDE; POVIDONE K25; FERRIC OXIDE RED; HYPROMELLOSE, UNSPECIFIED; LACTOSE MONOHYDRATE; POLYETHYLENE GLYCOL 6000; MAGNESIUM STEARATE; STARCH, CORN; POVIDONE K25; TALC; TITANIUM DIOXIDE

HIGHLIGHTS OF PRESCRIBING INFORMATION

These highlights do not include all the information needed to use NATAZIA safely and effectively. See full prescribing information for NATAZIA.
NATAZIA (estradiol valerate and
estradiol valerate/dienogest) tablets for oral use
Initial U.S. Approval: 2010

RECENT MAJOR CHANGES

Contraindications, Pregnancy (4) Removed 6/2024

WARNING: CIGARETTE SMOKING AND SERIOUS CARDIOVASCULAR EVENTS

See full prescribing information for complete boxed warning.

- Women over 35 years old who smoke should not use Natazia. (4)
- Cigarette smoking increases the risk of serious cardiovascular events from combination oral contraceptive (COC) use. (4)

1 INDICATIONS AND USAGE

- Natazia is a combination of dienogest , a progestin, and estradiol valerate, an estrogen, indicated for use by females of reproductive potential to prevent pregnancy. (1)
- The efficacy of Natazia in females of reproductive potential with a body mass index (BMI) of
  >30 kg/m^2 has not been evaluated. (1, 8.8)
- Treatment of heavy menstrual bleeding in females of reproductive potential without organic pathology who choose to use an oral contraceptive as their method of contraception. (1.2)

2 DOSAGE AND ADMINISTRATION

- Take one tablet daily by mouth at the same time every day. (2.1)
- Tablets must be taken in the order directed on the blister pack. (2.1)
- Do not skip or delay intake by more than 12 hours. (2.1)

3 DOSAGE FORMS AND STRENGTHS

Natazia consists of 28 film-coated, unscored tablets in the following order (3):

- 2 dark yellow tablets each containing 3 mg estradiol valerate
- 5 medium red tablets each containing 2 mg estradiol valerate and 2 mg dienogest
- 17 light yellow tablets each containing 2 mg estradiol valerate and 3 mg dienogest
- 2 dark red tablets each containing 1 mg estradiol valerate
- 2 white tablets (inert)

4 CONTRAINDICATIONS

- A high risk of arterial or venous thrombotic diseases (4)
- Undiagnosed abnormal uterine bleeding (4)
- Breast cancer (4)
- Liver tumors or liver disease (4)

5 WARNINGS AND PRECAUTIONS

- Vascular risks: Stop Natazia if a thrombotic event occurs. Stop Natazia at least 4 weeks before and through 2 weeks after major surgery. Start Natazia no earlier than 4 weeks after delivery, in women who are not breastfeeding. (5.1)
- Liver disease: Discontinue Natazia if jaundice occurs. (5.3)
- High blood pressure: Do not prescribe Natazia for women with uncontrolled hypertension or hypertension with vascular disease. (5.4)
- Carbohydrate and lipid metabolic effects: Monitor prediabetic and diabetic women taking Natazia. Consider an alternate contraceptive method for women with uncontrolled dyslipidemia. (5.6)
- Headache: Evaluate significant change in headaches and discontinue Natazia if indicated. (5.7)
- Uterine bleeding: Evaluate irregular bleeding or amenorrhea. (5.8)
- CYP3A4 induction: Women taking strong CYP3A4 inducers (for example, carbamazepine, phenytoin, rifampicin, and St. John’s wort) should not choose Natazia as their oral contraceptive due to the possibility of decreased contraceptive efficacy. (5.13, 7.1)

6 ADVERSE REACTIONS

The most common adverse reactions (≥ 2%) in clinical trials for Natazia are headache (including migraines) 13%, breast pain 7%, menstrual disorders 7%, nausea/vomiting 6%, acne 4%, mood changes (3%) and increased weight 3%. (6)

To report SUSPECTED ADVERSE REACTIONS, contact Bayer HealthCare Pharmaceuticals Inc. at 1-888-842-2937 or FDA at 1-800-FDA-1088 or www.fda.gov/medwatch

7 DRUG INTERACTIONS

Drugs or herbal products that induce certain enzymes (for example, CYP3A4) may decrease the effectiveness of COCs or increase breakthrough bleeding. Counsel patients to use a back-up or alternative method of contraception when enzyme inducers are used with COCs. (7.1)

8 USE IN SPECIFIC POPULATIONS

- Lactation: can decrease milk production. (8.2)
- Body Mass Index: The safety and efficacy of Natazia in women with a body mass index (BMI) of >30 kg/m^2 has not been evaluated. (8.8)

FULL PRESCRIBING INFORMATION

WARNING: CIGARETTE SMOKING AND SERIOUS CARDIOVASCULAR EVENTS

Cigarette smoking increases the risk of serious cardiovascular events from combination oral contraceptives (COC) use. This risk increases with age, particularly in women over 35 years of age, and with the number of cigarettes smoked. For this reason, COCs should not be used by women who are over 35 years of age and smoke. [See Contraindications (4).]

1 INDICATIONS AND USAGE

1.1 Oral Contraception

Natazia® is indicated for use by women to prevent pregnancy.

The efficacy of Natazia in women with a body mass index (BMI) of > 30 kg/m^2 has not been evaluated.

1.2 Heavy Menstrual Bleeding

Natazia is also indicated for the treatment of heavy menstrual bleeding in women without organic pathology who choose to use an oral contraceptive as their method of contraception [see Clinical Studies (14.2)].

2 DOSAGE AND ADMINISTRATION

2.1 How to Take Natazia

To achieve maximum contraceptive effectiveness, Natazia must be taken exactly as directed. Take one tablet by mouth at the same time every day. Tablets must be taken in the order directed on the blister pack. Tablets should not be skipped or intake delayed by more than 12 hours. For patient instructions for missed pills, see FDA-Approved Patient Labeling.

2.2 How to Start Natazia

Instruct the patient to begin taking Natazia on Day 1 of her menstrual cycle (that is, the first day of her menstrual bleeding). See FDA-Approved Patient Labeling. Instruct the patient to use a non-hormonal contraceptive as back-up during the first 9 days.

For postpartum women who do not breastfeed or after a second trimester abortion, start Natazia no earlier than 4 weeks postpartum due to the increased risk of thromboembolism. If the patient starts on Natazia postpartum and has not yet had a period, evaluate for possible pregnancy, and instruct her to use an additional method of contraception until she has taken Natazia for 9 consecutive days. The possibility of ovulation and conception prior to initiation of medication should also be considered.

If the patient is switching from a combination hormonal method such as:

  - Another pill
  - Vaginal ring
  - Patch
- Instruct her to take the first dark yellow pill on the first day of her withdrawal bleed. She should not continue taking the pills from her previous birth control pack. If she does not have a withdrawal bleed, rule out pregnancy before starting Natazia.
- If she previously used a vaginal ring or transdermal patch, she should start using Natazia on the day the ring or patch is removed.
- Instruct the patient to use a non-hormonal back-up method such as a condom or spermicide for the first 9 days.

If the patient is switching from a progestin-only method such as a:

  - Progestin-only pill
  - Implant
  - Intrauterine system
  - Injection
- Instruct her to take the first dark yellow pill on the day she would have taken her next progestin-only pill or on the day of removal of her implant or intrauterine system or on the day when she would have had her next injection.
- Instruct the patient to use a non-hormonal back-up method such as a condom or spermicide for the first 9 days.

2.3 Advice in case of Gastrointestinal Disturbances

In case of severe vomiting or diarrhea, absorption may not be complete and additional contraceptive measures should be taken. If vomiting or diarrhea occurs within 3-4 hours after taking a colored tablet, this can be regarded as a missed tablet.

3 DOSAGE FORMS AND STRENGTHS

Natazia (estradiol valerate and estradiol valerate/dienogest) tablets are available in blister packs.

Each blister pack contains 28 round, biconvex, film-coated tablets in the following order:

- 2 dark yellow tablets, with an embossed “DD” in a regular hexagon on one side, each containing 3 mg estradiol valerate
- 5 medium red tablets, with an embossed “DJ” in a regular hexagon on one side, each containing 2 mg estradiol valerate and 2 mg dienogest
- 17 light yellow tablets, with an embossed “DH” in a regular hexagon on one side, each containing 2 mg estradiol valerate and 3 mg dienogest
- 2 dark red tablets, with an embossed “DN” in a regular hexagon on one side, each containing 1 mg estradiol valerate
- 2 white tablets (inert), with an embossed “DT” in a regular hexagon on one side

4 CONTRAINDICATIONS

Natazia is contraindicated in females who are known to have or develop the following conditions:

- A high risk of arterial or venous thrombotic diseases. Examples include women who are known to:
  - Smoke, if over age 35 [see Boxed Warning and Warnings and Precautions (5.1)]
  - Have deep vein thrombosis or pulmonary embolism, now or in the past [see Warnings and Precautions (5.1)]
  - Have cerebrovascular disease [see Warnings and Precautions (5.1)]
  - Have coronary artery disease [see Warnings and Precautions (5.1)]
  - Have thrombogenic valvular or thrombogenic rhythm diseases of the heart (for example, subacute bacterial endocarditis with valvular disease, or atrial fibrillation) [see Warnings and Precautions (5.1)]
  - Have inherited or acquired hypercoagulopathies [see Warnings and Precautions (5.1)]
  - Have uncontrolled hypertension [see Warnings and Precautions (5.4)]
  - Have diabetes mellitus with vascular disease [see Warnings and Precautions (5.6)]
  - Have headaches with focal neurological symptoms or have migraine headaches with or without aura if over age 35 [see Warnings and Precautions (5.7)]
- Undiagnosed abnormal uterine bleeding [see Warnings and Precautions (5.8)]
- Current diagnosis of, or history of, breast cancer, which may be hormone sensitive [see Warnings and Precautions (5.2)]
- Liver tumors, benign or malignant, or liver disease [see Warnings and Precautions (5.3), Use in Specific Populations (8.7) and Clinical Pharmacology (12.3])].

5 WARNINGS AND PRECAUTIONS

5.1 Thromboembolic Disorders and Other Vascular Problems

Stop Natazia if an arterial or venous thrombotic event (VTE) occurs.

The use of COCs increases the risk of venous thromboembolism. However, pregnancy increases the risk of venous thromboembolism as much or more than the use of COCs. The risk of VTE in women using COCs has been estimated to be 3 to 9 per 10,000 woman-years. The risk of VTE is highest during the first year of use. Data from a large, prospective cohort safety study of various COCs suggest that this increased risk, as compared to that in non-COC users, is greatest during the first 6 months of COC use. Data from this safety study indicate that the greatest risk of VTE is present after initially starting a COC or restarting (following a 4 week or greater pill-free interval) the same or a different COC.

Use of COCs also increases the risk of arterial thromboses such as strokes and myocardial infarctions, especially in women with other risk factors for these events.

The risk of thromboembolic disease due to oral contraceptives gradually disappears after COC use is discontinued.

If feasible, stop Natazia at least 4 weeks before and through 2 weeks after major surgery or other surgeries known to have an elevated risk of thromboembolism.

Start Natazia no earlier than 4 weeks after delivery, in women who are not breastfeeding. The risk of postpartum thromboembolism decreases after the third postpartum week, whereas the risk of ovulation increases after the third postpartum week.

COCs have been shown to increase both the relative and attributable risks of cerebrovascular events (thrombotic and hemorrhagic strokes), although, in general, the risk is greatest among older (>35 years of age), hypertensive women who also smoke. COCs also increase the risk for stroke in women with other underlying risk factors.

Oral contraceptives must be used with caution in women with cardiovascular disease risk factors.

Stop Natazia if there is unexplained loss of vision, proptosis, diplopia, papilledema, or retinal vascular lesions. Evaluate for retinal vein thrombosis immediately. [See Adverse Reactions (6).]

5.2 Malignant Neoplasms

Breast Cancer

Natazia is contraindicated in females who currently have or have had breast cancer because breast cancer may be hormonally sensitive [see Contraindications (4)].

Epidemiology studies have not found a consistent association between use of combined oral contraceptives (COCs) and breast cancer risk. Studies do not show an association between ever (current or past) use of COCs and risk of breast cancer. However, some studies report a small increase in the risk of breast cancer among current or recent users (<6 months since last use) and current users with longer duration of COC use [see Adverse Reactions (6.2)].

Cervical Cancer

Some studies suggest that COCs are associated with an increase in the risk of cervical cancer or intraepithelial neoplasia. However, there is controversy about the extent to which these findings may be due to differences in sexual behavior and other factors.

5.3 Liver Disease

Discontinue Natazia if jaundice develops. Steroid hormones may be poorly metabolized in patients with impaired liver function. Acute or chronic disturbances of liver function may necessitate the discontinuation of COC use until markers of liver function return to normal and COC causation has been excluded.

Hepatic adenomas are associated with COC use. An estimate of the attributable risk is 3.3 cases/100,000 COC users. Rupture of hepatic adenomas may cause death through intra-abdominal hemorrhage.

Studies have shown an increased risk of developing hepatocellular carcinoma in long-term (> 8 years) COC users. However, the attributable risk of liver cancers in COC users is less than one case per million users.

Oral contraceptive-related cholestasis may occur in women with a history of pregnancy-related cholestasis. Women with a history of COC-related cholestasis may have the condition recur with subsequent COC use.

5.4 High Blood Pressure

For women with well-controlled hypertension, monitor blood pressure and stop Natazia if blood pressure rises significantly. Women with uncontrolled hypertension or hypertension with vascular disease should not use COCs.

An increase in blood pressure has been reported in women taking COCs, and this increase is more likely in older women and with extended duration of use. The incidence of hypertension increases with increasing concentration of progestin.

5.5 Gallbladder Disease

Studies suggest a small increased relative risk of developing gallbladder disease among COC users.

5.6 Carbohydrate and Lipid Metabolic Effects

Carefully monitor prediabetic and diabetic women who are taking Natazia. COCs may decrease glucose tolerance in a dose-related fashion.

Consider alternative contraception for women with uncontrolled dyslipidemia. A small proportion of women will have adverse lipid changes while on COCs.

Women with hypertriglyceridemia, or a family history thereof, may be at an increased risk of pancreatitis when using COCs.

5.7 Headache

If a woman taking Natazia develops new headaches that are recurrent, persistent, or severe, evaluate the cause and discontinue Natazia if indicated.

An increase in frequency or severity of migraine during COC use (which may be prodromal of a cerebrovascular event) may be a reason for immediate discontinuation of the COC.

5.8 Bleeding Irregularities

Breakthrough bleeding and spotting sometimes occur in patients on COCs, especially during the first three months of use. If bleeding persists or occurs after previously regular cycles, check for causes such as pregnancy or malignancy. If pathology and pregnancy are excluded, bleeding irregularities may resolve over time or with a change to a different COC.

Women who are not pregnant and use Natazia, may experience amenorrhea. Based on patient diaries, amenorrhea occurs in approximately 16% of cycles in women using Natazia. Pregnancy should be ruled out in the event of amenorrhea occurring in two or more consecutive cycles. Some women may encounter amenorrhea or oligomenorrhea after stopping COCs, especially when such a condition was pre-existent.

Based on patient diaries from three clinical trials evaluating the safety and efficacy of Natazia for contraception, 10-23% of women experienced intracyclic bleeding per cycle.

5.9 Depression

Women with a history of depression should be carefully observed and Natazia discontinued if depression recurs to a serious degree.

5.10 Interference with Laboratory Tests

The use of COCs may change the results of some laboratory tests, such as coagulation factors, lipids, glucose tolerance, and binding proteins. Women on thyroid hormone replacement therapy may need increased doses of thyroid hormone because serum concentrations of thyroid-binding globulin increase with use of COCs [see Clinical Pharmacology (12.3)].

5.11 Monitoring

A woman who is taking COCs should have a yearly visit with her healthcare provider for a blood pressure check and for other indicated healthcare.

5.12 Drug Interactions

Women who take medications that are strong cytochrome P450 3A4 (CYP3A4) inducers (for example, carbamazepine, phenytoin, rifampicin, and St. John’s wort) should not choose Natazia as their oral contraceptive while using these inducers and for at least 28 days after discontinuation of these inducers due to the possibility of decreased contraceptive efficacy [see Drug Interactions (7.1) and Clinical Pharmacology (12.3)].

5.13 Other Conditions

In women with hereditary angioedema, exogenous estrogens may induce or exacerbate symptoms of angioedema. Chloasma may occasionally occur, especially in women with a history of chloasma gravidarum. Women with a tendency to chloasma should avoid exposure to the sun or ultraviolet radiation while taking COCs.

6 ADVERSE REACTIONS

The following serious adverse reactions with the use of COCs are discussed elsewhere in the labeling:

- Serious cardiovascular events and stroke [see Boxed Warning and Warnings and Precautions (5.1)]
- Vascular events [see Warnings and Precautions (5.1)]
- Liver disease [see Warnings and Precautions (5.3)]

Adverse reactions commonly reported by COC users are:

- Irregular uterine bleeding
- Nausea
- Breast tenderness
- Headache

6.1 Clinical Trials Experience

Because clinical trials are conducted under widely varying conditions, adverse reaction rates observed in the clinical trials of a drug cannot be directly compared to rates in the clinical trials of another drug and may not reflect the rates observed in practice.

Contraception and Heavy Menstrual Bleeding Studies

A total of 2,131 women, 18 to 54 years of age, who took at least one dose of Natazia were enrolled in four clinical phase 3 trials. A total of 1,867 subjects were included in two clinical phase 3 studies with a treatment duration up to 28 cycles with Natazia as an oral contraceptive and 264 subjects in the two phase 3 clinical trials with a treatment duration of 7 cycles evaluating Natazia in the treatment of heavy, prolonged, and/or frequent menstrual bleeding in women without organic pathology [see Clinical Studies (14.1, 14.2)].

Adverse Reactions Leading to Study Discontinuation: 11.4% of the women discontinued from the clinical trials due to an adverse reaction; the most frequent adverse reactions leading to discontinuation were menstrual disorder (metrorrhagia, menorrhagia, menstruation irregular, genital hemorrhage, vaginal hemorrhage, dysfunctional uterine bleeding) (2.3%); mood changes (depression, mood swings, mood altered, depressed mood, dysthymic disorder, crying) (1.2%); acne (1.1%), headache (including migraines) (1.1%), and weight increased (0.7 %).

Common Adverse Reactions (≥ 2%): headache (including migraines) (12.7%), breast pain, discomfort or tenderness (7.0%), menstrual disorders (metrorrhagia, menstruation irregular, menorrhagia, vaginal hemorrhage, dysfunctional uterine bleeding, genital hemorrhage, abnormal withdrawal bleeding, uterine hemorrhage) (6.9%), nausea or vomiting (6.0%), acne (3.9%), mood changes (depression, mood swings, depressed mood, mood altered, affect lability, dysthymic disorder, crying) (3.0%) and increased weight (2.9%).

Serious Adverse Reactions: myocardial infarction (2 cases), ruptured ovarian cyst (2 cases), deep vein thrombosis, focal nodular hyperplasia of the liver, uterine leiomyoma, acute cholecystitis, and chronic acalculous cholecystitis.

6.2 Postmarketing Experience

Five studies that compared breast cancer risk between ever-users (current or past use) of COCs and never-users of COCs reported no association between ever use of COCs and breast cancer risk, with effect estimates ranging from 0.90 - 1.12 (Figure 1).

Three studies compared breast cancer risk between current or recent COC users (<6 months since last use) and never users of COCs (Figure 1). One of these studies reported no association between breast cancer risk and COC use. The other two studies found an increased relative risk of 1.19–1.33 with current or recent use. Both of these studies found an increased risk of breast cancer with current use of longer duration, with relative risks ranging from 1.03 with less than one year of COC use to approximately 1.4 with more than 8–10 years of COC use.

Figure 1: Relative Studies of Risk of Breast Cancer with Combined Oral Contraceptives.

RR = relative risk; OR = odds ratio; HR = hazard ratio. “ever COC” are females with current or past COC use; “never COC use” are females that never used COCs.

The following adverse reactions have been identified during post-approval use of Natazia. Because these reactions are reported voluntarily from a population of uncertain size, it is not always possible to reliably estimate their frequency or establish a causal relationship to drug exposure.

Vascular disorders: Venous and arterial thromboembolic events (including pulmonary emboli, deep vein thrombosis, cerebral thrombosis, myocardial infarction and stroke), hypertension

Hepatobiliary disorders: Gallbladder disease, hepatitis

Immune system disorders: Hypersensitivity

Metabolism and nutrition disorders: Fluid retention, hypertriglyceridemia

Nervous system disorders: Dizziness

Skin and subcutaneous tissue disorders: Chloasma, angioedema, erythema nodosum, erythema multiforme

Gastrointestinal disorders: Gastrointestinal symptoms (for example, abdominal pain)

Infections and infestations: Vulvovaginal candidiasis

7 DRUG INTERACTIONS

Consult the labeling of all concurrently-used drugs to obtain further information about interactions with hormonal contraceptives or the potential for enzyme alterations.

7.1 Effects of Other Drugs on Combined Oral Contraceptives

Substances diminishing the efficacy of COCs: Dienogest is a substrate of CYP3A4. Women who take medications that are strong CYP3A4 inducers should not choose Natazia as their oral contraceptive while using these inducers and for at least 28 days after discontinuation of these inducers due to the possibility of increased breakthrough bleeding and/or decreased contraceptive efficacy.

Drugs or herbal products that induce certain enzymes, including CYP3A4, may decrease the effectiveness of COCs or increase breakthrough bleeding. Some drugs or herbal products that may decrease the effectiveness of hormonal contraceptives include phenytoin, barbiturates, carbamazepine, bosentan, felbamate, griseofulvin, oxcarbazepine, rifampin, topiramate and products containing St. John’s wort. Interactions between oral contraceptives and other drugs may lead to breakthrough bleeding and/or contraceptive failure. Counsel women to use an alternative method of contraception or a back-up method when enzyme inducers are used with COCs, and to continue back-up contraception for 28 days after discontinuing the enzyme inducer to ensure contraceptive reliability.

Multiple dose co-administration of the strong CYP3A4 inducer rifampin with estradiol valerate/dienogest tablets in healthy postmenopausal women led to a decrease in dienogest and estradiol systemic exposure at steady state. [See Clinical Pharmacology (12.3).]

Substances Increasing the Systemic Exposure of COCs (enzyme inhibitors): Concomitant administration of moderate or strong CYP3A4 inhibitors like azole antifungals (for example, ketoconazole, itraconazole, voriconazole, fluconazole), verapamil, macrolides (for example, clarithromycin, erythromycin), diltiazem, and grapefruit increase the serum concentrations of both estradiol and dienogest.

In a multiple dose study investigating the effect of CYP3A4 inhibitors (ketoconazole and erythromycin) on Natazia, steady state estradiol and dienogest exposures were increased when co-administered with ketoconazole or erythromycin [see Clinical Pharmacology (12.3)].

Human Immunodeficiency Virus (HIV)/Hepatitis C Virus (HCV) Protease Inhibitors and Non-Nucleoside Reverse Transcriptase Inhibitors: Significant changes (increase and decrease) in plasma concentrations of estrogen and progestin have been noted in some cases of co-administration of HIV/HCV protease inhibitors or with non-nucleoside reverse transcriptase inhibitors.

Antibiotics: There have been reports of pregnancy while taking hormonal contraceptives and antibiotics, but clinical pharmacokinetic studies have not shown consistent effects of antibiotics on plasma concentrations of synthetic steroids.

7.2 Effects of Combined Oral Contraceptives on Other Drugs

COCs containing ethinyl estradiol may inhibit the metabolism of other compounds. COCs have been shown to significantly decrease plasma concentrations of lamotrigine, likely due to induction of lamotrigine glucuronidation. This may reduce seizure control; therefore, dosage adjustments of lamotrigine may be necessary. Consult the labeling of the concurrently-used drug to obtain further information about interactions with COCs or the potential for enzyme alterations. [See Clinical Pharmacology (12.3).]

Women on thyroid hormone replacement therapy may need increased doses of thyroid hormone because serum concentrations of thyroid-binding globulin increase with use of COCs.

7.3 Interference with Laboratory Tests

The use of contraceptive steroids may influence the results of certain laboratory tests, such as coagulation factors, lipids, glucose tolerance, and binding proteins [see Warnings and Precautions (5.11) and Drug Interactions (7.2)].

8 USE IN SPECIFIC POPULATIONS

8.1 Pregnancy

Risk Summary

There is no reason to use COCs in pregnancy Discontinue Natazia if pregnancy occurs. Epidemiologic studies and meta-analyses have not found an increased risk of genital or non-genital birth defects (including cardiac anomalies and limb-reduction defects) following exposure to COCs prior to conception or during early pregnancy.

In the U.S. general population, the estimated background risk of major birth defects and miscarriage in clinically recognized pregnancies is 2 to 4 percent and 15 to 20 percent, respectively.

8.2 Lactation

Risk Summary

Contraceptive hormones and/or metabolites are present in human milk. CHCs can reduce milk production in breastfeeding females. This reduction can occur at any time but is less likely to occur once breastfeeding is well-established. When possible, advise the nursing female to use other forms of contraception until she discontinues breastfeeding. [See also Dosage and Administration (2.2)]. The developmental and health benefits of breastfeeding should be considered along with the mother’s clinical need for Natazia and any potential adverse effects on the breast-fed child from Natazia or from the underlying maternal condition.

8.4 Pediatric Use

Safety and efficacy of Natazia have been established in women of reproductive age. Efficacy is expected to be the same for postpubertal adolescents under the age of 18 and for users 18 years and older. Use of this product before menarche is not indicated.

8.5 Geriatric Use

Natazia has not been studied in postmenopausal women and is not indicated in this population.

8.6 Patients with Renal Impairment

The pharmacokinetics of Natazia has not been studied in subjects with renal impairment, but an effect requiring dose adjustment is unlikely to be present [see Clinical Pharmacology (12.3)].

8.7 Patients with Hepatic Impairment

The pharmacokinetics of Natazia has not been studied in subjects with hepatic impairment. Steroid hormones may be poorly metabolized in patients with impaired liver function. Acute or chronic disturbances of liver function may necessitate the discontinuation of COC use until markers of liver function return to normal. [See Contraindications (4) and Warnings and Precautions (5.3)].

8.8 Body Mass Index

The safety and efficacy of Natazia in women with a BMI of > 30 kg/m^2 has not been evaluated.

10 OVERDOSAGE

There have been no reports of serious ill effects from overdose, including ingestion by children. Overdosage may cause withdrawal bleeding in females and nausea.

11 DESCRIPTION

Natazia (estradiol valerate and estradiol valerate/dienogest) tablets provide an oral contraceptive regimen consisting of 26 active film-coated tablets that contain the active ingredients specified for each tablet below, followed by two inert film-coated tablets:

- 2 dark yellow tablets each containing 3 mg estradiol valerate
- 5 medium red tablets each containing 2 mg estradiol valerate and 2 mg dienogest
- 17 light yellow tablets each containing 2 mg estradiol valerate and 3 mg dienogest
- 2 dark red tablets each containing 1 mg estradiol valerate
- 2 white tablets (inert)

Natazia also contains the excipients lactose monohydrate, maize starch, maize starch pre-gelatinized, povidone 25, magnesium stearate, hypromellose, macrogol 6000, talc, titanium dioxide, and ferric oxide pigment, yellow, or ferric oxide pigment, red.

The empirical formula of estradiol valerate is C23 H32 O3 and the chemical structure is:

Estradiol Valerate

The chemical name of estradiol valerate is Estra-1,3,5(10)-triene-3,17-diol(17ß)-,17-pentanoate.

The empirical formula of dienogest is C20 H25 NO2 and the chemical structure is:

Dienogest

The chemical name of dienogest is (17α)-17-Hydroxy-3-oxo-19-norpregna-4,9-diene-21-nitrile.

12 CLINICAL PHARMACOLOGY

12.1 Mechanism of Action

COCs lower the risk of becoming pregnant primarily by suppressing ovulation.

12.2 Pharmacodynamics

The estrogen in Natazia is estradiol valerate, a synthetic prodrug of 17ß-estradiol.

The progestin in Natazia is dienogest (DNG). DNG displays properties of 19-nortestosterone derivatives as well as properties associated with progesterone derivatives.

Cardiac Electrophysiology

The effect of Natazia on QT prolongation was evaluated in a randomized, double-blind, positive (moxifloxacin 400 mg) and negative (placebo) controlled crossover study in healthy subjects. A total of 53 subjects were administered Natazia (containing 3 mg dienogest and 2 mg estradiol valerate), dienogest 10 mg, and placebo as once daily doses for 4 days, and moxifloxacin 400 mg as a single oral dose. The upper bound of the 90% confidence interval for the largest placebo-adjusted, baseline-corrected QTc based on Fridericia’s correction method (QTcF) was below 10 msec, the threshold for regulatory concern.

12.3 Pharmacokinetics

Absorption

After oral administration of estradiol valerate, cleavage to 17β-estradiol and valeric acid takes place during absorption by the intestinal mucosa or in the course of the first liver passage. This gives rise to estradiol and its metabolites, estrone and other metabolites. Maximum serum estradiol concentrations of 73.3 pg/mL are reached at a median of approximately 6 hours (range: 1.5–12 hours) and the area under the estradiol concentration curve [AUC(0–24h)] was 1301 pg·h/mL after single ingestion of a tablet containing 3 mg estradiol valerate under fasted condition on Day 1 of the 28-day sequential regimen.

Bioavailability of dienogest is about 91%. Maximum serum dienogest concentrations of 91.7 ng/mL are reached at a median of approximately 1 hour (range: 0.5–1.5 hour) and the area under the dienogest concentration curve [AUC(0–24h)] was 964 ng/mL after single oral administration of Natazia tablet containing 2 mg estradiol valerate/3 mg dienogest under fasted condition. The pharmacokinetics of dienogest are dose-proportional within the dose range of 1–8 mg. Steady state is reached after 4 days of the same dosage of 2 mg dienogest. The mean accumulation ratio for AUC (0–24h) is approximately 1.24.

The mean plasma pharmacokinetic parameters at steady state following repeated oral doses of a 2 mg estradiol valerate/3 mg dienogest combination tablet in fertile women under fasted condition are reported in Table 1.

Table 1 Arithmetic Mean (SD) Serum Pharmacokinetic Parameters at Steady-state (on Day 24) following Repeated Oral Doses of 2 mg EV/3 mg DNG on Days 8-24 of the 28 day Regimen in Fertile Women under Fasted Condition (N=15)
Parameter | Dienogest | Estradiol | Estrone
Cmax [Cmax = Maximum serum concentration] | 85.2 (19.7) ng/ml | 70.5 (25.9) pg/ml | 483 (198) pg/ml
Tmax [Tmax = Time to reach maximum concentration] (h) [Median (range) for Tmax] | 1.5 (1–2) | 3 (1.5–12) | 4 (3–12)
AUC [AUC(0-24h) = Area under the concentration-time curve from 0 h data point up to 48 h post-administration] (0–24h) | 828 (187) ng·h/ml | 1323 (480) pg·h/ml | 7562 (3403) pg·h/ml
t½ (h) | 12.3 (1.4) | NA [NA: Data not available] | NA

Food Effect

Concomitant food intake in women resulted in a 28% decrease for dienogest Cmax and 23% increase of estradiol Cmax while the exposure (AUC) of both dienogest and estradiol did not change.

Distribution

In serum, 38% of estradiol is bound to sex hormone-binding globulin (SHBG), 60% to albumin and 2–3% circulates in free form. An apparent volume of distribution of approximately 1.2 L/kg was determined after intravenous (IV) administration.

A relatively high fraction (10%) of circulating dienogest is present in the free form, with approximately 90% being bound non-specifically to albumin. Dienogest does not bind to SHBG and corticosteroid-binding globulin (CBG). The volume of distribution at steady state (Vd,ss) of dienogest is 46 L after the IV administration of 85 mcg ^3H-dienogest.

Metabolism

After oral administration of estradiol valerate, approximately 3% of the dose is directly bioavailable as estradiol. Estradiol undergoes an extensive first-pass effect and a considerable part of the dose administered is already metabolized in the gastrointestinal mucosa. The CYP 3A family is known to play the most important role in human estradiol metabolism. Together with the pre-systemic metabolism in the liver, about 95% of the orally administered dose becomes metabolized before entering the systemic circulation. The main metabolites are estrone and its sulfate or glucuronide conjugates.

Dienogest is extensively metabolized by the known pathways of steroid metabolism (hydroxylation, conjugation), with the formation of endocrinologically mostly inactive metabolites. CYP3A4 was identified as a predominant enzyme catalyzing the metabolism of dienogest.

Excretion

Estradiol and its metabolites are mainly excreted in urine, with about 10% being excreted in the feces. The terminal half-life of estradiol is approximately 14 hours.

Dienogest is mainly excreted renally in the form of metabolites and unchanged dienogest is the dominating fraction in plasma. The terminal half-life of dienogest is approximately 11 hours.

Use in Specific Populations

Pediatric Use: Safety and efficacy of Natazia has been established in women of reproductive age. Efficacy is expected to be the same for postpubertal adolescents under the age of 18 and for users 18 years and older. Use of this product before menarche is not indicated.

Geriatric Use: Natazia has not been studied in postmenopausal women and is not indicated in this population.

Renal Impairment: The pharmacokinetics of Natazia has not been studied in subjects with renal impairment.

Hepatic Impairment: The pharmacokinetics of Natazia has not been studied in subjects with hepatic impairment. Steroid hormones may be poorly metabolized in patients with impaired liver function. Acute or chronic disturbances of liver function may necessitate the discontinuation of COC use until markers of liver function return to normal. [See Contraindications (4) and Warnings and Precautions (5.3).]

Body Mass Index: The efficacy of Natazia in women with a BMI of > 30 kg/m^2 has not been evaluated.

Drug Interactions

Consult the labeling of all concurrently used drugs to obtain further information about interactions with oral contraceptives or the potential for enzyme alterations.

Effects of Other Drugs on Combined Oral Contraceptives

Substances diminishing the efficacy of COCs: Dienogest is a substrate of CYP3A4. Drugs or herbal products that induce certain enzymes, including CYP3A4, may decrease the effectiveness of COCs or increase breakthrough bleeding.

The effect of the CYP3A4 inducer rifampin was studied in an open-label, non-randomized, single center study in 16 healthy postmenopausal women. All volunteers received a treatment regimen of 2 mg estradiol valerate and 3 mg dienogest combination tablets, dosed once daily over 17 days, and of rifampin, which was administered once daily in an oral dose of 600 mg on Days 12 to 16. Twenty-four-hour (24h) pharmacokinetics of estradiol and dienogest on Days 11 and 17 were compared. Co-administration of rifampin with estradiol valerate/dienogest tablets led to a 52 % and 83% decrease in the mean Cmax and AUC(0–24h), respectively, for dienogest and a 25% and 44% decrease in Cmax and AUC(0–24h), respectively, for estradiol at steady state.

Substances Increasing the Systemic Exposure of COCs (enzyme inhibitors): The effect of a strong CYP3A4 inhibitor, ketoconazole, on dienogest and estradiol exposure was studied in an open-label, one-sequence, one-way crossover study in healthy postmenopausal Caucasian women. One tablet of 2 mg estradiol valerate and 3 mg dienogest was administered orally once a day for 14 days. Twelve volunteers received an oral dose of 400 mg ketoconazole (that is, 2 tablets containing 200 mg ketoconazole) once daily for 7 days (Days 8–14). Twenty-four hour pharmacokinetics of estradiol and dienogest on Days 7 and 14 were compared. Co-administration with the strong inhibitor ketoconazole increased the AUC (0–24h) at steady state for dienogest and estradiol by 2.86 and 1.57-fold, respectively. There was also a 1.94 and 1.65-fold increase of Cmax at steady state for dienogest and estradiol when co-administered with ketoconazole.

The effect of a moderate CYP3A4 inhibitor, erythromycin, on dienogest and estradiol exposure was studied in an open-label, one-sequence, one-way crossover study in healthy postmenopausal Caucasian women. One tablet of 2 mg estradiol valerate and 3 mg dienogest was administered orally once a day for 14 days. Twelve volunteers received an oral dose of 500 mg erythromycin three times a day for 7 days (Days 8–14). Twenty-four hour pharmacokinetics of estradiol and dienogest on Days 7 and 14 were compared. When co-administered with the moderate inhibitor erythromycin, the AUC (0–24h) of dienogest and estradiol at steady state were increased by 1.62 and 1.33-fold, respectively. There was also a 1.33 and 1.51-fold increase of Cmax at steady state for dienogest and estradiol, respectively, when co-administered with erythromycin.

HIV/HCV Protease Inhibitors and non-nucleoside reverse transcriptase inhibitors: Significant changes (increase or decrease) in the plasma concentrations of the estrogen and progestin have been noted in some cases of co-administration of HIV/HCV protease inhibitors or with non-nucleoside reverse transcriptase inhibitors.

Antibiotics: There have been reports of pregnancy while taking hormonal contraceptives and antibiotics, but clinical pharmacokinetic studies have not shown consistent effects of antibiotics on plasma concentrations of synthetic steroids.

Effects of Combined Oral Contraceptives on Other Drugs

COCs containing ethinyl estradiol may inhibit the metabolism of other compounds. COCs have been shown to significantly decrease plasma concentrations of lamotrigine, likely due to induction of lamotrigine glucuronidation. This may reduce seizure control; therefore, dosage adjustments of lamotrigine may be necessary. Consult the labeling of the concurrently-used drug to obtain further information about interactions with COCs or the potential for enzyme alterations.

In vitro studies with human CYP enzymes did not indicate an inhibitory potential of dienogest at clinically relevant concentrations.

Women on thyroid hormone replacement therapy may need increased doses of thyroid hormone because serum concentration of thyroid-binding globulin increases with use of COCs.

13 NONCLINICAL TOXICOLOGY

13.1 Carcinogenesis, Mutagenesis, Impairment of Fertility

In a 24-month carcinogenicity study in mice dosed orally with dienogest by gavage with doses of 5, 15 and 50 mg/kg/day (males) and 10, 30 and 100 mg/kg/day (females), the systemic exposures in the females were 1.1, 3.5, and 10.6 times the exposure (AUC of dienogest) of women taking a 3 mg dose. A statistically significantly higher incidence of stromal polyps of the uterus was observed in females given 100 mg/kg. In a similar study in rats given 1, 3, and 10 mg/kg for 104 weeks, 0.2, 1.4, and 6.1 times the exposure of women taking a 3 mg dose, there were no statistically significant drug-related neoplasms [see Warnings and Precautions (5.2, 5.3)].

Dienogest was not mutagenic in in vitro reverse mutation tests in bacteria, in chromosome aberration tests in human peripheral lymphocytes, mouse lymphoma cells, and Chinese hamster lung cells, and tests of unscheduled DNA synthesis (UDS) in rat and human liver cells. Dienogest was also negative in an in vivo mouse micronucleus test, a rat liver initiation-promotion model, and an in vitro/in vivo UDS test in female rats.

14 CLINICAL STUDIES

14.1 Oral Contraceptive Clinical Trials

The study conducted in North America (U.S. and Canada) was a multicenter, open-label, single-arm, unintended pregnancy study. There were 490 healthy subjects between 18 and 35 years of age (mean age: 25.1 years) who were treated for up to 28 cycles of 28 days each. The racial demographic of enrolled women was: Caucasian (76%), Hispanic (13%), African-American (7%), Asian (3%), and Other (1%). The weight range for treated women was 40 to 100 kg (mean weight: 62.5 kg) and the BMI range was 14 to 30 kg/m^2 (mean BMI: 23.3 kg/m^2). Of treated women, 15% discontinued the study treatment due to an adverse event, 13% were lost to follow up, 10% withdrew their consent, 8% discontinued due to other reason, 1% discontinued due to protocol deviation, and 1% discontinued due to pregnancy.

The study conducted in Europe (Germany, Austria and Spain) was a multicenter, open-label, single-arm contraceptive reliability study. There were 1,377 healthy subjects between 18 and 50 years of age (mean age: 30.3 years) who were treated for 20 cycles of 28 days each. The racial demographic of enrolled women was predominantly Caucasian (99.2%). The weight range for treated women was 38 to 98 kg (mean weight: 63.8 kg) and the BMI range was 15 to 31.8 kg/m^2 (mean BMI: 22.8 kg/m^2). Of treated women, 10% discontinued the study treatment due to an adverse event, 5% discontinued due to other reason, 2% were lost to follow up, 2% discontinued due to protocol deviation, 2% withdrew their consent, and 1% discontinued due to pregnancy.

The Pearl Index (PI) was the primary efficacy endpoint used to assess contraceptive reliability and was assessed in each of the two studies, assuming all subjects were at risk of pregnancy in all medication cycles unless back-up contraception was documented. The PI is based on pregnancies that occurred after the onset of treatment and within 7 days after the last pill intake. Cycles in which conception did not occur, but which included the use of back-up contraception, were not included in the calculation of the PI. The PI also includes patients who did not take the drug correctly. The estimated PI for the North American study is 1.64 and the estimated PI for the European study is 1.04. The Kaplan-Meier method was also used to calculate the contraceptive failure rate.

The summary of the Pearl Indexes and cumulative contraceptive failure rates are provided in Table 2:

Table 2: Summary of the Pearl Indexes and the Cumulative Contraceptive Failure Rates
Study | Age Group | Relative Treatment Exposure Cycles [Total treatment exposure time without back-up contraception] | Number of Pregnancies within 13 Cycles and 7 Days after Last Treatment | Pearl Index | Upper Limit of 95% CI | Contraceptive Failure Rate at the End of First Year
North America | 18–35 | 3,969 | 5 | 1.64 | 3.82 | 0.016
Europe | 18–35 | 11,275 | 9 | 1.04 | 1.97 | 0.010

14.2 Heavy Menstrual Bleeding Clinical Trials

The efficacy and safety of Natazia were evaluated in two multi-regional, multicenter, double-blind, randomized, placebo-controlled clinical trials. Study 308960 was performed in the United States and Canada and Study 308961 was performed in Australia and 9 European countries. The studies were identical in design. The studies enrolled women, 18 years of age or older, with a diagnosis of dysfunctional uterine bleeding characterized as heavy, prolonged and/or frequent bleeding without organic pathology. Heavy menstrual bleeding (HMB) was defined as menstrual blood loss of 80 mL or more in at least 2 bleeding episodes. The diagnosis of HMB was documented through the collection of used sanitary protection (pads and tampons) to quantify blood loss assessed by the alkaline hematin method. Overall, about 85% of the subjects qualified for the study because they had heavy menstrual bleeding symptoms.

A total of 421 women with a mean age of 38.2 and a mean BMI of 25.5 were randomized to the two clinical studies, for a total of 269 women in the Natazia group and 152 women in the placebo group, and treated for seven 28-day cycles. Approximately 81% were Caucasian, 13% were Black, and 6% were Hispanic or Asian or Other.

The primary efficacy variable was the proportion of subjects who were completely relieved of symptoms, which was defined by the number of subjects with the absence of any dysfunctional bleeding symptom and who met up to 8 strictly defined criteria for success during the 90-day efficacy assessment phase. In Study 308960, the proportion of the intent-to-treat subjects with complete symptom relief was 29.2% in the Natazia group compared to 2.9% in the placebo group. In Study 308961, the proportion of the intent-to-treat subjects with complete symptom relief was 29.5% in the Natazia group compared to 1.2% in the placebo group.

In both studies, Natazia was effective in treating the symptoms of HMB in the subset of women who entered the study with symptoms specific to HMB. Among patients with HMB, menstrual blood loss (MBL) was statistically significantly reduced in the group treated with Natazia compared with placebo (p<0.0001 for both studies). Evaluating data based on 28-day cycles, the median menstrual blood volume at Cycle 7 was reduced from the baseline median by 90% in one trial and 87% in the other. For women treated with placebo, the median menstrual blood volume at Cycle 7 was reduced from the baseline median by 14% and 32% in the two trials, respectively. Figures 2 and 3 display the MBL volume by cycle and by study.

Figure 2: Median Menstrual Blood Loss Volume by Cycle (Study 308960)
Figure 3: Median Menstrual Blood Loss Volume by Cycle (Study 308961)

16 HOW SUPPLIED/STORAGE AND HANDLING

16.1 How Supplied

Natazia (estradiol valerate and estradiol valerate/dienogest) tablets are available in packages of three blister packs (NDC 50419-409-03).

The active and inert film-coated tablets are rounded with biconvex faces, one side is embossed with a regular hexagon shape with the letters DD or DJ or DH or DN or DT.

Each blister pack (28 film-coated tablets) contains in the following order:

- 2 round biconvex dark yellow film-coated tablets with embossed “DD” in a regular hexagon on one side each containing 3 mg estradiol valerate
- 5 round biconvex medium red film-coated tablets with embossed “DJ” in a regular hexagon on one side each containing 2 mg estradiol valerate and 2 mg dienogest
- 17 round biconvex light yellow film-coated tablets with embossed “DH” in a regular hexagon on one side each containing 2 mg estradiol valerate and 3 mg dienogest
- 2 round biconvex dark red film-coated tablets with embossed “DN” in a regular hexagon on one side each containing 1 mg estradiol valerate
- 2 white round biconvex white film-coated tablets with embossed “DT” in a regular hexagon on one side (inert)

16.2 Storage

Store at 25º C (77º F); excursions permitted to 15–30oC (59–86oF) [see USP Controlled Room Temperature].

17 PATIENT COUNSELING INFORMATION

See “FDA-approved patient labeling (Patient Information).”

- Counsel patients that cigarette smoking increases the risk of serious cardiovascular events from COC use, and that women who are over 35 years old and smoke should not use COCs.
- Counsel patients that the increased risk of VTE compared to non-users of COCs is greatest after initially starting a COC or restarting (following a 4 week or greater pill-free interval) the same or a different COC.
- Counsel patients that Natazia does not protect against HIV infection (AIDS) and other sexually transmitted diseases.
- Counsel patients on Warnings and Precautions associated with COCs.
- Inform patients that Natazia is not indicated during pregnancy. If pregnancy occurs during treatment with Natazia, instruct the patient to stop further intake.
- Counsel patients to take one tablet daily by mouth at the same time every day in the exact order noted on the blister. Instruct patients what to do in the event pills are missed. See What Should I Do if I Miss any Pills section in FDA-Approved Patient Labeling.
- Counsel women who are taking strong CYP3A4 inducers (for example, carbamazepine, phenytoin, rifampicin, and St. John’s wort) not to choose Natazia as their oral contraceptive due to the possibility of decreased contraceptive efficacy.
- Counsel patients to use a back-up or alternative method of contraception when weak or moderate enzyme inducers are used with Natazia.
- Counsel patients who are breastfeeding or who desire to breastfeed that COCs may reduce breast milk production. This is less likely to occur if breastfeeding is well established.
- Counsel any patient who starts COCs postpartum, and who has not yet had a period, to use an additional method of contraception until she has taken Natazia for 9 consecutive days.
- Counsel patients that amenorrhea may occur. Rule out pregnancy in the event of amenorrhea in two or more consecutive cycles.

FDA-Approved Patient Labeling

Guide for Using Natazia

WARNING TO WOMEN WHO SMOKE

Do not use Natazia if you smoke cigarettes and are over 35 years old. Smoking increases your risk of serious cardiovascular side effects (heart and blood vessel problems) from birth control pills, including death from heart attack, blood clots or stroke. This risk increases with age and the number of cigarettes you smoke.

Birth control pills help to lower the chances of becoming pregnant when taken as directed. They do not protect against HIV infection (AIDS) and other sexually transmitted diseases.

What Is Natazia?

Natazia is a birth control pill. It contains two female hormones, an estrogen called estradiol valerate and a progestin called dienogest. Estradiol valerate is a synthetic estrogen that is converted to estradiol in your body.

Natazia is used to treat heavy menstruation (your monthly period) that is not caused by any diagnosed conditions of the uterus (womb) in women who decide to use an oral contraceptive for birth control. Talk to your healthcare provider to determine if your bleeding is heavier than normal.

How Does Natazia Work?

Birth control pills prevent your ovaries from producing and releasing mature eggs. Natazia decreases menstrual bleeding by thinning the lining of the uterus.

How Well Does Natazia Work For Contraception?

Your chance of getting pregnant depends on how well you follow the directions for taking your birth control pills. The better you follow the directions, the less chance you have of getting pregnant.

Based on the results of two clinical studies, 1 to 2 women out of 100 women may get pregnant during the first year they use Natazia.

The following chart shows the chance of getting pregnant for women who use different methods of birth control. Each box on the chart contains a list of birth control methods that are similar in effectiveness. The most effective methods are at the top of the chart. The box on the bottom of the chart shows the chance of getting pregnant for women who do not use birth control and are trying to get pregnant.

How Well Does Natazia Work For Heavy Menstrual Bleeding?

In two clinical trials in women with heavy menstrual bleeding who were treated with Natazia, their menstrual bleeding was reduced by an average of 90% in one trial and 87% in the other. For women treated with placebo, their menstrual bleeding was reduced by an average of 14% and 32% in the two trials, respectively.

How Do I Take Natazia?

- Take one pill every day at the same time. Take the pills in the order directed on the blister pack.
- Do not skip pills or delay taking your pill by more than 12 hours. If you miss pills (including starting the pack late), you could get pregnant. The more pills you miss, the more likely you are to get pregnant.
- If you have trouble remembering to take Natazia, talk to your healthcare provider about how to make pill-taking easier, or about using another method of birth control.
- You may have spotting or light bleeding when you first take Natazia. Spotting or light bleeding is normal at first.
- You may feel sick to your stomach (nauseous), especially during the first few months that you take Natazia. If you feel sick to your stomach, do not stop taking the pill. The problem will usually go away. If your nausea doesn't go away, call your healthcare provider.
- If you vomit or have diarrhea within 4 hours of taking your pill, follow the instructions for “What Should I Do if I Miss any Pills.”
- Missing pills can also cause spotting or light bleeding, even when you take the missed pills later. On the days you take 2 pills to make up for missed pills, you could also feel a little sick to your stomach.

Before you start taking Natazia

- Decide what time of day you want to take your pill. It is important to take it at the same time every day and in the order as directed on the blister pack.

- Look at your Natazia blister pack. The blister pack has 4 rows of 7 pills each, for a total of 28 pills. Find:
- where on the pack to start taking your pills
- in what order to take the pills

Each NATAZIA blister pack has 28 pills

- 2 dark yellow pills with hormones, for Days 1 and 2
- 5 medium red pills with hormones for Days 3–7
- 17 light yellow pills with hormones for Days 8–24
- 2 dark red pills with hormones for Days 25 and 26
- 2 white pills without hormones for Days 27 and 28
- After taking the last white pill (day 28) of the blister pack, start taking the first dark yellow pill from a new blister pack the very next day whether or not you are having your period.
- Be sure to have ready at all times another kind of birth control (such as condoms and spermicides) to use as a back-up in case you miss pills.
- It is not uncommon to miss a period. However, if you miss 2 periods in a row or feel like you may be pregnant, call your healthcare provider. If you are pregnant, you should stop taking Natazia.
When to Start Natazia

If you start taking Natazia and you did not use a hormonal birth control method before:

- Take the first dark yellow pill on the first day (Day 1) of your natural menstrual cycle. The first day of your menstrual cycle is the first day you start spotting or bleeding.
- Use non-hormonal back-up contraception such as a condom and spermicide for the first 9 days that you take Natazia.

If you start taking Natazia and you are switching from a combination hormonal method such as:

- another pill
- vaginal ring
- patch
- Take the first dark yellow pill on the first day of your period. Do not continue taking the pills from your previous birth control pack. If you do not have a period, contact your healthcare provider before you start Natazia.
- If you previously used a vaginal ring or transdermal patch, you should start using Natazia on the day the ring or patch is removed.
- Use a non-hormonal back-up method such as a condom and spermicide for the first 9 days you take Natazia.

If you start taking Natazia and you are switching from a progestin-only method such as a:

- progestin-only pill
- implant
- intrauterine system
- injection
- Take the first dark yellow pill on the day you would have taken your next progestin-only pill or on the day of removal of your implant or intrauterine system or on the day when you would have had your next injection.
- Use a non-hormonal back-up method such as a condom and spermicide for the first 9 days you take Natazia.

What Should I Do if I Miss any Pills

If you forgot to start a new blister pack, you may already be pregnant. Use back-up contraception (such as condoms and spermicides) anytime you have sex. Call your healthcare provider if you are unsure whether you are pregnant.

- Do not take more than 2 pills in one day. On the days you take 2 pills to make up for missed pills, you may feel a little sick to your stomach (nauseous).
- If you start vomiting or have diarrhea within 4 hours of taking your pill, take another pill of the same color from your extra blister pack.

If you are less than 12 hours late taking your pill

- Take your pill as soon as you remember.
- Take the next pill at the usual time.
- You do not need to use back-up contraception.

If you miss ONE PILL for more than 12 hours

Days 1–17

- Take your missed pill immediately.
- Take your next pill at the usual time (you may have to take two pills that day).
- Use back-up contraception for the next 9 days.
- Continue taking one pill each day at the same time for the rest of your cycle.

Days 18–24

- Do not take any pills from your current blister pack and throw the pack away.
- Take Day 1 pill from a new blister pack.
- Use back-up contraception for the next 9 days.
- Continue taking one pill from the new blister pack at the same time each day.

Days 25–28

- Take your missed pill immediately.
- Take your next pill at the usual time (you may have to take two pills that day).
- No back-up contraception is needed.
- Continue taking one pill each day at the same time for the rest of your cycle.

If you miss TWO PILLS in a row

Days 1–17
(if you miss the pills for Days 17 and 18, follow the instructions for Days 17–25 instead)

- Do not take the missed pills. Instead, take the pill for the day on which you first noticed you had missed pills.
- Use back-up contraception for the next 9 days.
- Continue taking one pill each day at the same time for the rest of your cycle.

Days 17–25
(if you miss the pills for Days 25 and 26, follow the instructions for Days 25–28 instead)

- Do not take any pills from your current blister pack and throw the pack away.
- Take Day 3 pill from a new blister pack.
- Use back-up contraception for the next 9 days.
- Continue taking one pill from the new blister pack at the same time each day.

Days 25–28

- Do not take any pills from your current blister pack and throw the pack away.
- Start a new pack on the same day or start a new pack on the day you usually start a new pack.
- No back-up contraception is needed.
- Continue taking one pill from the new pack at the same time each day, for the rest of your cycle.

You may already be pregnant or COULD BECOME PREGNANT if you had sex on the days after the pills were missed. The more pills missed and the closer they are to the end of the cycle, the higher the risk of a pregnancy. You should call your healthcare provider if you are unsure whether you are already pregnant.

If you are still not sure of what to do about the pills you have missed:

- Call your healthcare provider
- Use back-up contraception (such as condoms and spermicides) anytime you have sex and keep taking 1 pill each day

Who Should Not Take Natazia?

Your healthcare provider will not give you Natazia if you have:

- Ever had breast cancer which may be sensitive to female hormones
- Liver disease, including liver tumors
- Ever had blood clots in your arms, legs, or lungs
- Ever had a stroke
- Ever had a heart attack
- Certain heart valve problems or heart rhythm abnormalities that can cause blood clots to form in the heart
- An inherited problem with your blood that makes it clot more than normal
- High blood pressure that medicine can't control
- Diabetes with kidney, eye, or blood vessel damage
- Certain kinds of severe migraine headaches with aura, numbness, weakness or changes in vision

If any of these conditions happen for the first time while using Natazia, stop taking Natazia right away and talk to your healthcare provider. You should use non-hormonal contraceptive measures when you stop using Natazia.

Also, do not take birth control pills if you:

- Smoke and are over 35 years old
- Are pregnant
- Have any unexplained bleeding from the vagina

Birth control pills may not be a good choice for you if you have ever had jaundice (yellowing of the skin or eyes) caused by pregnancy (also called cholestasis of pregnancy).

What Else Should I Know about Taking Natazia?

Birth control pills do not protect you against any sexually transmitted disease, including HIV, the virus that causes AIDS.

Do not skip any pills, even if you do not have sex often.

If you miss a period, you could be pregnant. However, some women miss periods or have light periods on birth control pills, even when they are not pregnant. Contact your healthcare provider for advice if you:

- Think you are pregnant
- Miss one period and have not taken your birth control pills according to directions
- Miss two periods in a row

Birth control pills should not be taken during pregnancy. However, birth control pills taken by accident during pregnancy are not known to cause birth defects.

If you are breastfeeding, consider another birth control method until you are ready to stop breastfeeding. Birth control pills that contain estrogen, like Natazia, may decrease the amount of milk you make. A small amount of the pill's hormones pass into breast milk.

If you have vomiting or diarrhea, your birth control pills may not work as well. Use another birth control method, like condoms and a spermicide, until you check with your healthcare provider.

If you are scheduled for any laboratory tests, tell your healthcare provider you are taking birth-control pills. Certain blood tests may be affected by birth-control pills.

Tell your healthcare provider about all medicines and herbal products that you take, including prescription and over-the-counter medicines, vitamins and herbal supplements.

Natazia may affect the way other medicines work, and other medicines may affect how well Natazia works. Know the medicines you take.

Keep a list of them to show your healthcare provider and pharmacist when you get a new medicine. You should not choose Natazia as your birth control pill if you take carbamazepine, phenytoin, rifampicin or St. John's wort, because these medicines may make Natazia ineffective.

What are the Most Serious Risks of Taking Birth Control Pills?

Like pregnancy, birth control pills increase the risk of serious blood clots, especially in women who have other risk factors, such as smoking, obesity, or age greater than 35. This increased risk is highest when you first start taking birth control pills and when you restart the same or different birth control pills after not using them for a month or more.

It is possible to die from a problem caused by a blood clot, such as a heart attack or a stroke. Some examples of serious blood clots are blood clots in the:

- Legs (deep vein thrombosis)
- Lungs (pulmonary embolus)
- Eyes (loss of eyesight)
- Heart (heart attack)
- Brain (stroke)

A few women who take birth control pills may get:

- High blood pressure
- Gallbladder problems
- Rare cancerous or noncancerous liver tumors
All of these events are uncommon in healthy women.

Call your healthcare provider right away if you have:

- Persistent leg pain
- Sudden shortness of breath
- Sudden blindness, partial or complete
- Severe pain in your chest
- Sudden, severe headache unlike your usual headaches
- Weakness or numbness in an arm or leg, or trouble speaking
- Yellowing of the skin or eyeballs
What are the Common Side Effects of Birth Control Pills?

The most common side effects of birth control pills are:

- Spotting or bleeding between menstrual periods
- Nausea
- Breast tenderness
- Headache

These side effects are usually mild and usually disappear with time.

Less common side effects are:

- Acne
- Less sexual desire
- Bloating or fluid retention
- Blotchy darkening of the skin, especially on the face
- High blood sugar, especially in women who already have diabetes
- High fat levels in the blood
- Depression, especially if you have had depression in the past.

Call your healthcare provider immediately if you have any thoughts of harming yourself.

- Problems tolerating contact lenses
- Weight changes

This is not a complete list of possible side effects. Talk to your healthcare provider if you develop any side effects that concern you. You may report side effects to the FDA at 1-800-FDA-1088.

No serious problems have been reported from a birth control pill overdose, even when accidentally taken by children.

Do Birth Control Pills Cause Cancer?

It is not known if hormonal birth control pills causes breast cancer. Some studies, but not all, suggest that there could be a slight increase in the risk of breast cancer among current users with longer duration of use.

If you have breast cancer now, or have had it in the past, do not use hormonal birth control because some breast cancers are sensitive to hormones.

Women who use birth control pills may have a slightly higher chance of getting cervical cancer. However, this may be due to other reasons such as having more sexual partners.

What Should I Know about My Period when Taking Natazia?

Irregular vaginal bleeding or spotting may occur while you are taking Natazia. Irregular bleeding may vary from slight staining between menstrual periods to breakthrough bleeding, which is a flow much like a regular period. Irregular bleeding occurs most often during the first few months of oral contraceptive use, but may also occur after you have been taking the pill for some time. Such bleeding may be temporary and usually does not indicate any serious problems. It is important to continue taking your pills on schedule. If the bleeding occurs in more than one cycle, is unusually heavy, or lasts for more than a few days, call your healthcare provider.

Also, your menstrual period while using oral contraceptives may be shorter and lighter than usual. Some women may not have a menstrual period but this should not be cause for alarm as long has you have taken the pills according to direction.

What if I Miss My Scheduled Period when Taking Natazia?

It is not uncommon to miss your period. However, if you miss more than two periods in a row or miss one period when you have not taken your birth control pills according to directions, call your healthcare provider. Also notify your healthcare provider if you have symptoms of pregnancy such as morning sickness or unusual breast tenderness. It is important that your healthcare provider checks you to find out if you are pregnant. Stop taking Natazia if you are pregnant.

What If I Want to Become Pregnant?

You may stop taking the pill whenever you wish. Consider a visit with your healthcare provider for a pre-pregnancy checkup before you stop taking the pill.

General Advice about Natazia

Your healthcare provider prescribed Natazia for you. Please do not share Natazia with anyone else. Keep Natazia out of the reach of children.

If you have concerns or questions, ask your healthcare provider. You may also ask your healthcare provider for a more detailed label written for medical professionals.

Revised 6/2024

Manufactured for:

Bayer HealthCare Pharmaceuticals Inc.
Whippany, NJ 07981

Manufactured in Germany

© 2023, Bayer HealthCare Pharmaceuticals Inc.
All Rights Reserved.

Bayer HealthCare Pharmaceuticals Inc.

PACKAGE LABEL

Natazia Trade Carton

NDC 50419-409-01
1 Unit

Rx only

This product (like all oral contraceptives) is
intended to prevent pregnancy. It does not protect
against HIV infection (AIDS) and other sexually
transmitted diseases.

Natazia
estradiol valerate 3 mg, 1 mg tablets
estradiol valerate/dienogest 2 mg/2 mg, 2mg/3 mg tablets

28 tablets
oral